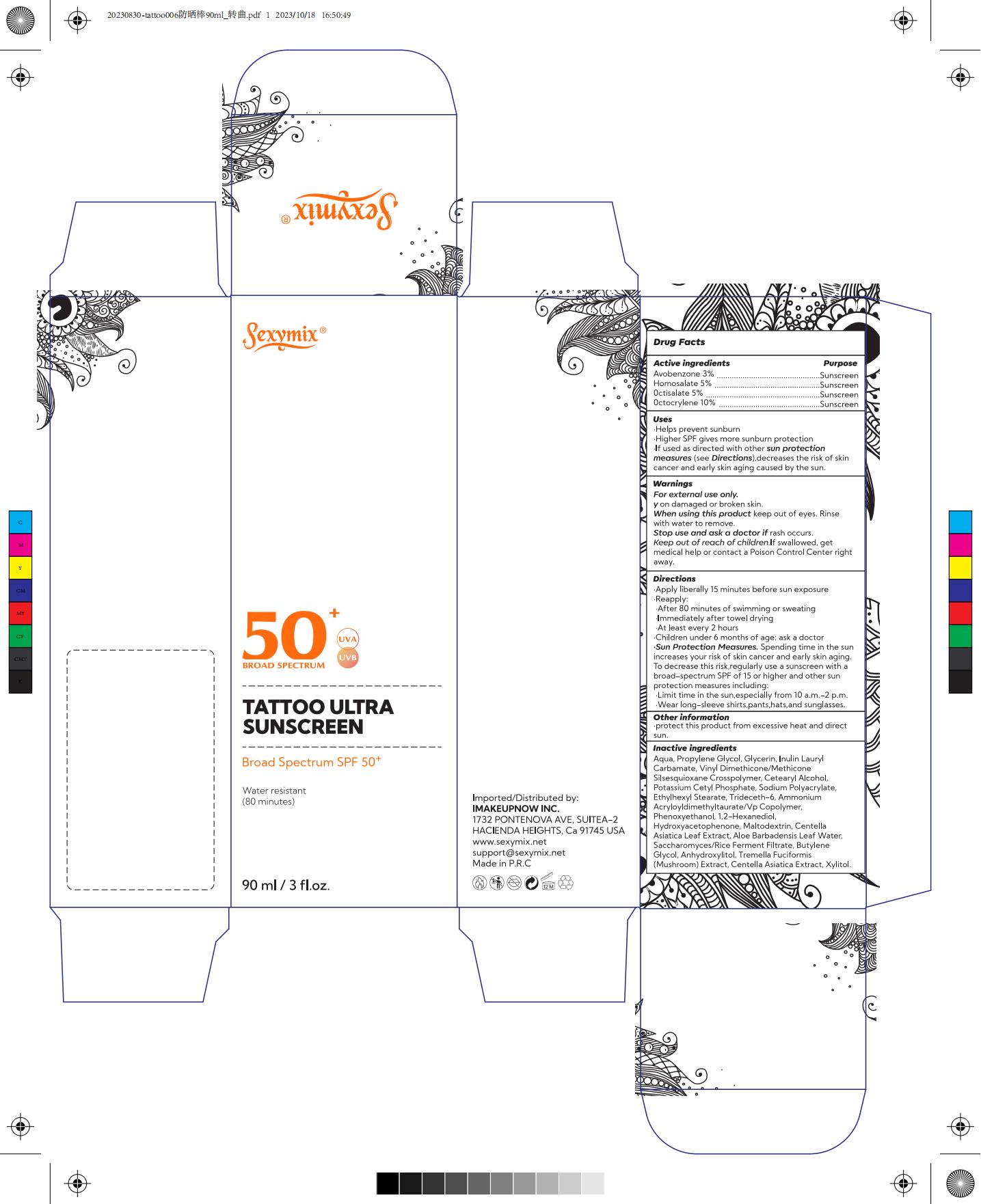 DRUG LABEL: SEXY MIX Tattoo Ultra Sunscreen Broad Spectrum SPF 50
NDC: 82723-005 | Form: CREAM
Manufacturer: Aopline Health Industry Technology (Guangzhou) Co., Ltd.
Category: otc | Type: HUMAN OTC DRUG LABEL
Date: 20250108

ACTIVE INGREDIENTS: AVOBENZONE 3 mg/100 mL; HOMOSALATE 5 mg/100 mL; OCTISALATE 5 mg/100 mL; OCTOCRYLENE 10 mg/100 mL
INACTIVE INGREDIENTS: XYLITOL; HYDROXYACETOPHENONE; VINYL DIMETHICONE/METHICONE SILSESQUIOXANE CROSSPOLYMER; WATER; PROPYLENE GLYCOL; CETOSTEARYL ALCOHOL; POTASSIUM CETYL PHOSPHATE; SODIUM POLYACRYLATE (8000 MW); ETHYLHEXYL STEARATE; TRIDECETH-6; AMMONIUM ACRYLOYLDIMETHYLTAURATE/VP COPOLYMER; PHENOXYETHANOL; 1,2-HEXANEDIOL; ANHYDROXYLITOL; MALTODEXTRIN; BUTYLENE GLYCOL; CENTELLA ASIATICA LEAF; ALOE VERA LEAF; GLYCERIN; CENTELLA ASIATICA TRITERPENOIDS; INULIN LAURYL CARBAMATE

82723-005
SEXY MIX Tattoo Ultra Sunscreen Broad Spectrum SPF 50

Active Ingredients

Avobenzone 3%
Homosalate 5%
0ctisalate 5%
0ctocrylene 10%

Purpose

purpose: sunscreen

Uses

Helps prevent sunburn
Higher SPF gives more sunburn protection
If used as directed with other sun protection
measures (see Directions) , decreases the risk of skin
cancer and early skin aging caused by the sun

Warnings

For external use only .
y on damaged or broken skin
When using this product keep out of eyes , Rinse
with water to remove
Stop use and ask a doctor if rash occurs
Keep out of reach of children . If swallowed , get
medical help or contact a Poison Control Center right
away .

Directions

Apply liberally 15 minutes before sun exposure
Reapplly :
After 80 minutes of swimming or sweating
Immediately after towel drying
At least every 2 hours
Children under 6 months of age : ask a doctor
Sun Protection Measures . Spending time in the sun
increases your risk of skin cancer and early skin aging
To decrease this risk , regularly use a sunscreen with a
broad-spectrum SPF of 15 or higher and other sun
protection measures including :
Limit time in the sun , especially from 10 a m . -2 p m
Wear long-sleeve shirts , pants , hats , and sunglasses .

Other Information

protect this product from excessive heat and direct sun

Inactive Ingredients

Aqua, Propylene Glycol, Glycerin, Inulin Laury
Carbamate, Vinyl Dimethicone/Methicone
Silsesquioxane Crosspolymer, Cetearyl Alcohol,
Potassium Cetyl Phosphate, Sodium Polyacrylate,
Ethylhexyl Stearate, Trideceth-6, Ammonium
Acryloyldimethyltaurate/Vp Copolymer,
Phenoxyethanol, 1, 2-hexanediol
Hydroxyacetophenone, Maltodextrin, Centella
Asiatica Leaf Extract Aloe Barbadensis Leaf Water
Saccharomyces/ice Ferment Filtrate, Butylene
Glycol, Anhydroxylitol, Tremella Fuciformis
(Mushroom)Extract, Centella Asiatica Extract, Xylitol

Keep out of reach of children . If swallowed , get
medical help or contact a Poison Control Center right
away .

Stop use

When using this product keep out of eyes , Rinse
with water to remove
Stop use and ask a doctor if rash occurs
Keep out of reach of children . If swallowed , get
medical help or contact a Poison Control Center right
away .

When using this product keep out of eyes , Rinse
with water to remove
Stop use and ask a doctor if rash occurs

Do not use on damaged or broken skin
When using this product keep out of eyes . Rinse with
water to remove
Stop use and ask a doctor if rash occurs
Keep out of reach of children . If swallowed , get medical
help or contact a Poison Control Center right away .

Package Label

82723-005 TATTOO ULTRA SUNSCREEN